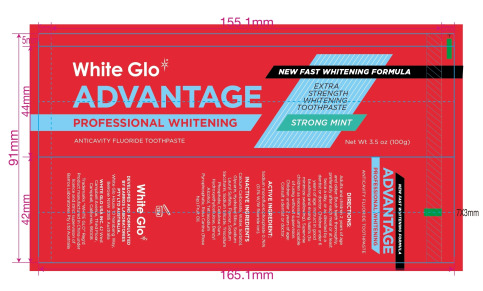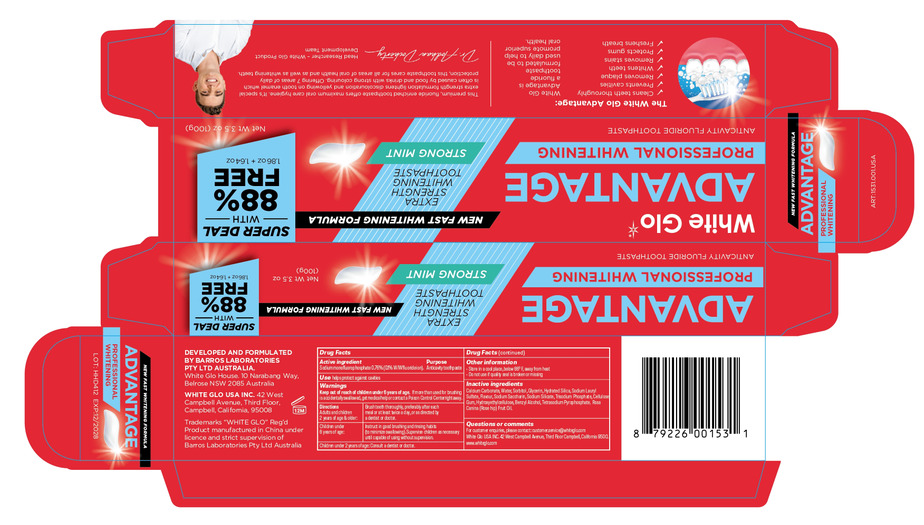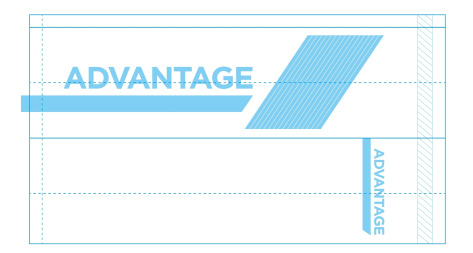 DRUG LABEL: Professional  whitening tooth
NDC: 82168-004 | Form: PASTE
Manufacturer: Guangzhou City Caiye Cosmetics CO., Ltd
Category: otc | Type: HUMAN OTC DRUG LABEL
Date: 20241212

ACTIVE INGREDIENTS: SODIUM MONOFLUOROPHOSPHATE 0.76 g/100 g
INACTIVE INGREDIENTS: BENZYL ALCOHOL; SODIUM SACCHARIN; HYDROXYETHYLCELLULOSE; CALCIUM CARBONATE; WATER; SORBITOL; SILICA; SODIUM LAURYL SULFATE; GLYCERIN; CELLULOSE GUM; SODIUM SILICATE; TETRASODIUM PYROPHOSPHATE

82168-004

Active Ingredient(s)

Sodium monofluorophosphate 0.76%

Purpose

Anticavity tothpaste

Use

Use helps protect against cavities

Warnings

Keep out of reach of children under 6 years of age. If more than used for brushing is
acidentally sallowed, get medical help or contact a Poison Control Center right away.

Do not use on open skin wounds

WHEN USING

Please keep away from your eyes when using this product

STOP USE

If in contact with the eyes, rinse thoroughly with water.

Keep out of reach of children under 6 years of age.

Directions

Adults and children 2 years of age & older: Brush teth thoroughly, preferably after each meal or at least twice a day, or as directed by
a dentist or doctor.
Children under 6 years of age: Instruct in good brushing and rinsing habits (to minimize swallowing). Supervise children as necessary

until capable of using without supervision,

Children under 2 years of age: Consult a dentist or doctor.

Other information

Store in a cool place below 86° F away from heat
Do not use if quality seal is broken or missing

Inactive ingredients

Calium Carbonate, Water, Sorbitol, Glycerin, Hydrated Silica, Sodium Lauryl
Sulfate, Aawour, Sodium Saccharin, Sodium Silicate, Trisodium Phosphate, Cellulose
Gum, Hydroyethylollulose, Benzyl Alcohol, Tetrasodium Pyrophosphate, Rosa
Canina (Rose hip) Fruit 0il.